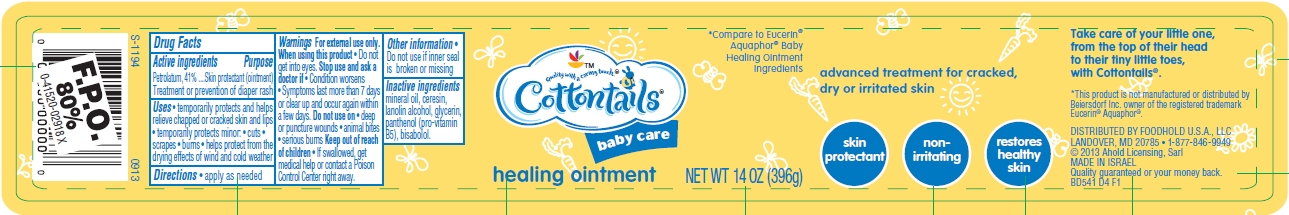 DRUG LABEL: Baby Care Healing
NDC: 41520-540 | Form: OINTMENT
Manufacturer: American Sales Company
Category: otc | Type: HUMAN OTC DRUG LABEL
Date: 20130930

ACTIVE INGREDIENTS: PETROLATUM 41 g/100 g
INACTIVE INGREDIENTS: MINERAL OIL; CERESIN; LANOLIN; ALCOHOL; GLYCERIN; PANTHENOL; LEVOMENOL

Cottontails Baby Care Healing Ointment

Active ingredient

Petrolatum 41%

Purpose

Skin protectant (ointment)

Treatment or prevention of diaper rash

Uses

- temporarily protects and helps relive chapped or cracked skin and lips
- temporarily protects minor:
  cuts
  scrapes
  burns
- helps protect from the drying effects of wind and cold weather

Warnings

For external use only.

When using this product

- Do not get into eyes.

Stop use and ask a doctor if

- Condition worsens
- Symptoms last more than 7 days or clear up and occur again within a few days.

Do not use on

- deep or puncture wounds
- animal bites
- serious burns

If swallowed, get medical help or contact a Poison Control Center right away.

Directions

apply as needed

Other information

Do not use if inner seal is broken or missing

Inactive ingredients

mineral oil, ceresin, lanolin alcohol, glycerin, panthenol (pro-vitamin B5), bisabolol.

Package/Label Principal Display Panel

Cottontails baby care

healing ointment

*Compare to Eucerin® Aquaphor ® Baby Healing Ointment Ingredients

NET WT 14 OZ (396g)

advanced treatment for cracked, dry or irritated skin

skin protectant

non-irritating

restores healthy skin

Take care of your little one, from the top of their head to their tiny little toes, with Cottontails©.

This product is not manufactured or distributed by Beiersdorf Inc. owner of the registered trademark Eucerin® Aquaphor®.

DISTRIBUTED BY FOODHOLD U.S.A., LLC
LANDOVER, MD 20785 1-877-846-9949
© 2013 Ahold Licensing, Sarl
MADE IN ISRAEL
Quality guaranteed or your money back.
BD541 D4 F1

Jar Label